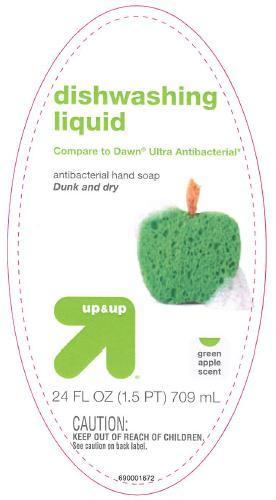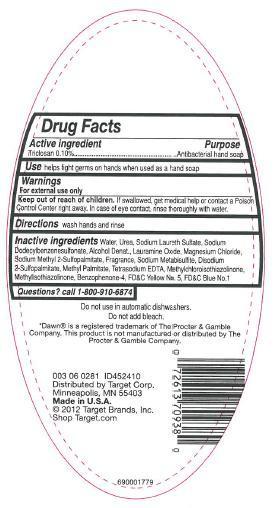 DRUG LABEL: Up (and) Up Green Apple Scent
NDC: 63691-019 | Form: SOAP
Manufacturer: Sun Products Corporation
Category: otc | Type: HUMAN OTC DRUG LABEL
Date: 20151223

ACTIVE INGREDIENTS: TRICLOSAN 0.1 g/100 mL
INACTIVE INGREDIENTS: WATER; UREA; SODIUM DODECYLBENZENESULFONATE; SODIUM LAURETH SULFATE; ALCOHOL; MAGNESIUM CHLORIDE; LAURAMINE OXIDE; DISODIUM 2-SULFOPALMITATE; METHYL PALMITATE; SODIUM METABISULFITE; EDETATE SODIUM; METHYLCHLOROISOTHIAZOLINONE; METHYLISOTHIAZOLINONE; SULISOBENZONE; FD&C YELLOW NO. 5; FD&C BLUE NO. 1

Active ingredient

Triclosan 0.10%

INDICATIONS AND USAGE

Use helps fight germs on hands when used as a hand soap

WARNINGS

For external use only

Keep out of reach of children. If swallowed, get medical help or contact a Poison Control Center right away. In case of eye contact, rinse thoroughly with water.

DOSAGE AND ADMINISTRATION

Directions wash hands and rinse

PURPOSE

Antibacterial hand soap

INACTIVE INGREDIENT

Inactive ingredients Water, Urea, Sodium Laureth Sulfate, Sodium Dodecylbenzenesulfonate, Alcohol Denat., Lauramine Oxide, Magnesium Chloride, Sodium Methyl 2-Sulfopalmitate, Fragrance, Sodium Metabisulfite, Disodium 2-Sulfopalmitate, Methyl Palmitate, Tetrasodium EDTA, Methylchloroisothiazolinone, Methylisothiazolinone, Benzophenone-4, Yellow No. 5, Blue No.1

Questions? call 1-800-910-6874

PACKAGE LABEL

LBLFR

LBLBK